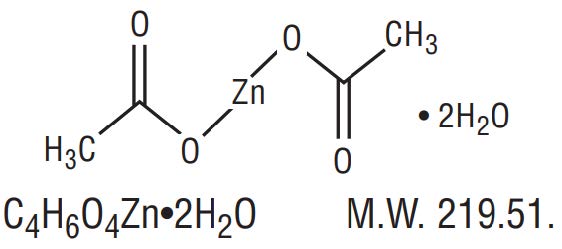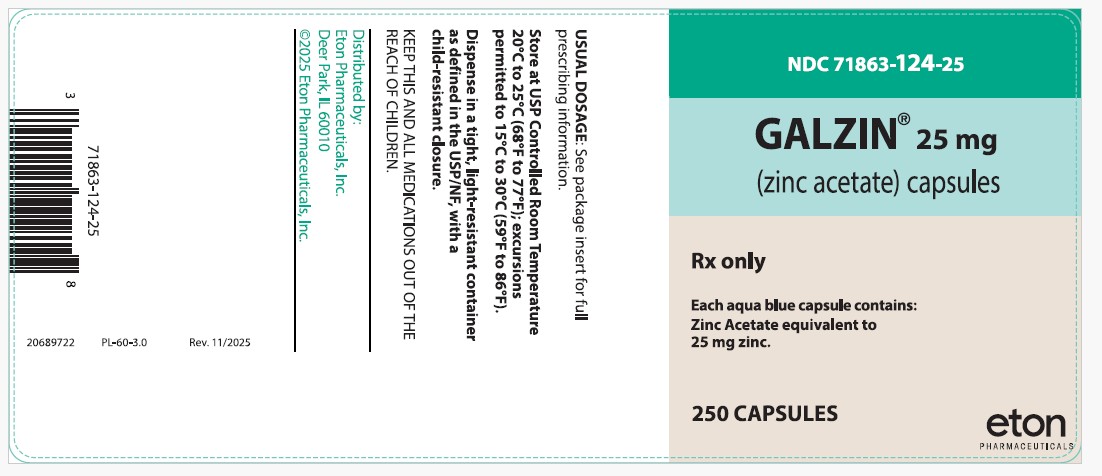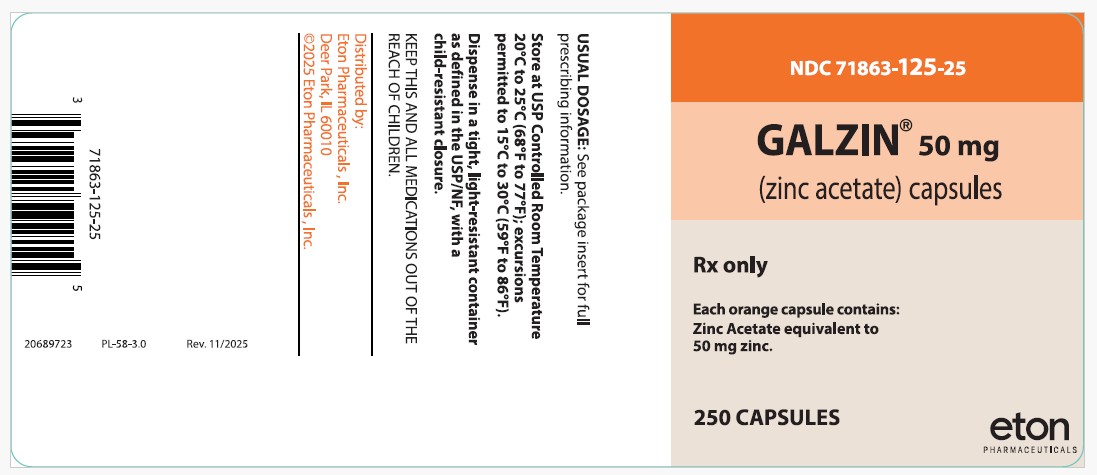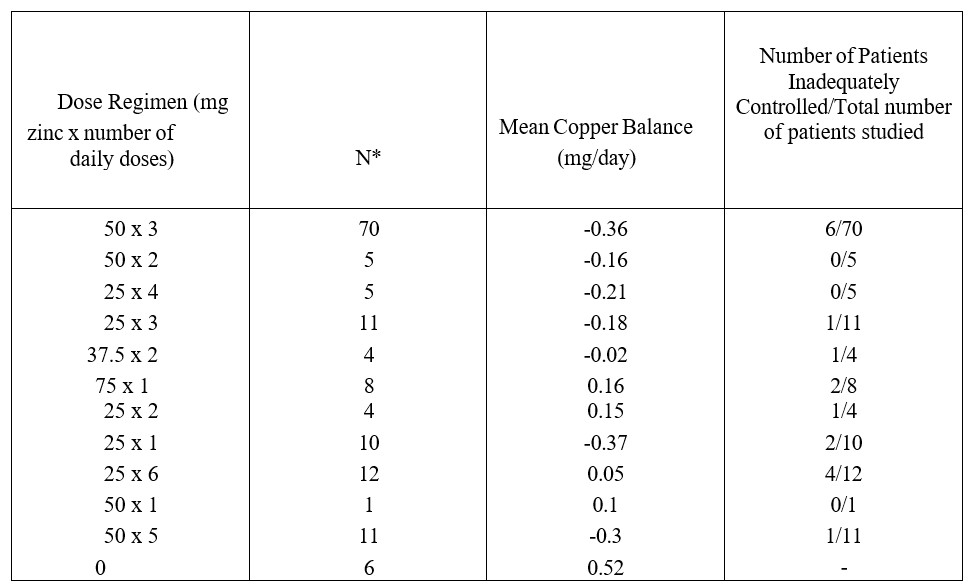 DRUG LABEL: GALZIN
NDC: 71863-124 | Form: CAPSULE, GELATIN COATED
Manufacturer: Eton Pharmaceuticals, Inc.
Category: prescription | Type: HUMAN PRESCRIPTION DRUG LABEL
Date: 20251112

ACTIVE INGREDIENTS: ZINC ACETATE 25 mg/1 1
INACTIVE INGREDIENTS: STARCH, CORN; SHELLAC; FERROSOFERRIC OXIDE; FD&C BLUE NO. 2; FD&C BLUE NO. 1; D&C YELLOW NO. 10; MAGNESIUM STEARATE; TITANIUM DIOXIDE; FD&C RED NO. 40; PROPYLENE GLYCOL; GELATIN, UNSPECIFIED

GALZIN® (Zinc Acetate) Capsules DESCRIPTION

Zinc acetate as the dihydrate is a salt of zinc used to inhibit the absorption of copper in patients with Wilson's disease. Its structural formula is:

Zinc acetate occurs as white crystals or granules, freely soluble in water and in boiling alcohol, and slightly soluble in alcohol.
GALZIN® (Zinc Acetate) Capsules contain the equivalent of 25 or 50 mg of zinc, in addition to corn starch and magnesium stearate in gelatin capsules. The 25 mg capsule shells contain titanium dioxide and the 50 mg capsule shells contain titanium dioxide, methylparaben and propylparaben. The 25 mg capsule shells contain FD&C Blue #1; the 50 mg capsule shells contain FD&C Red #40, D&C Red #28, and D&C Yellow #10.

CLINICAL PHARMACOLOGY

Introduction

Wilson's disease (hepatolenticular degeneration) is an autosomal recessive metabolic defect in hepatic excretion of copper in the bile, resulting in accumulation of excess copper in the liver, and subsequently in other organs, including the brain, kidneys, eyes, bone, and muscles. In this disease, hepatocytes store excess copper, but when their capacity is exceeded copper is released into the blood and is taken up in extrahepatic sites, such as the brain, resulting in motor disorders (ataxia, tremors, speech difficulties) and psychiatric manifestations (irritability, depression, deterioration of work performance). Redistribution of excess copper in hepatocytes leads to hepatocellular injury, inflammation, necrosis, and eventual cirrhosis. Patients may present clinically with predominantly hepatic, neurologic, or psychiatric symptoms.

The disease has been treated by restricting copper in the diet, and the use of chelating agents to bind free copper to reduce its toxicity and facilitate its excretion. The purpose of initial treatment of symptomatic patients with a chelating agent is to detoxify copper. Once the patient's symptoms have stabilized clinically, maintenance treatment begins. Clinical measures are used to determine whether the patient remains stable (See PRECAUTIONS: Monitoring Patients).

The active moiety in zinc acetate is zinc cation. Regardless of the ligand, zinc blocks the intestinal absorption of copper from the diet and the reabsorption of endogenously secreted copper such as that from the saliva, gastric juice and bile. Zinc induces the production of metallothionein in the enterocyte, a protein that binds copper thereby preventing its serosal transfer into the blood. The bound copper is then lost in the stool following desquamation of the intestinal cells.

Pharmacokinetics

Because the proposed site of action of zinc is an effect on copper uptake at the level of the intestinal cell, pharmacokinetic evaluations based on blood levels of zinc do not provide useful information on zinc bioavailability at the site of action. Determinations of zinc content in the liver and the plasma zinc concentration after the oral administration of zinc acetate have yielded inconsistent results. However, foods and beverages have been shown to decrease the uptake of zinc thereby decreasing the levels of zinc in the plasma of healthy volunteers. For this reason, the oral dose of zinc should be separated from food and beverages, other than water, by at least one hour.

Pharmacodynamics

In pharmacodynamic studies, the methods used included net copper balance and radiolabeled copper uptake in Wilson’s disease patients. These studies showed that a regimen of 50 mg t.i.d. of zinc acetate was effective in inducing a negative mean copper balance (-0.44 mg/day) and an adequate mean 64Cu uptake (0.82% of the administered dose). A regimen of 25 mg t.i.d. of zinc acetate was also pharmacodynamically active but fewer patients have been treated with this regimen than 50 mg t.i.d.

CLINICAL TRIALS

In the single center United States trial, 60 patients with Wilson’s disease (31 male, 29 female) who had adequate detoxification of copper after initial chelation therapy were entered into a copper balance study of various dose regimens of zinc acetate. Patients were hospitalized to carefully control food and liquid intake. Food, urine and feces were analyzed for copper content, and copper balance was defined as the difference between copper intake and copper elimination/excretion over a 10-day period. A patient was considered in adequate copper balance if the result was less than +0.25 mg copper/day. Results for the groups in each dose regimen tested and for adequacy of individual results are provided in the following table.

*N = number of copper balance studies. Some patients had more than one balance study, at different doses or at the same dose at widely separated intervals.

While all zinc acetate regimens appeared better than no therapy, there was little experience with doses other than 50 mg t.i.d. Once daily dosing did not appear to give satisfactory control in many cases, and would be inadequate in patients with poor compliance. Based on the limited data available 25 mg t.i.d. was also thought to be an adequate dose regimen, and not shown to be inferior to 50 mg t.i.d. Dose related toxicity was not found in this study.

Symptomatic Patients Initially Treated With a Chelating Drug

Clinical parameters such as neuropsychiatric status including evaluation of speech, and liver function tests were followed as the patients continued therapy on an adequate zinc acetate dose regimen. One hundred and thirty-three patients were followed for up to 14 years. There was no deterioration of neuropsychiatric function including speech and biochemical liver function tests, including bilirubin, transaminases, alkaline phosphatase and lactic dehydrogenase. The liver function tests remained either within normal range or slightly above the upper limit of normal for up to 9 years of treatment.

Pre-symptomatic Patients

In this study 30 pre-symptomatic patients were followed for up to 10 years. Diagnosis of the pre-symptomatic Wilson’s disease was made on the basis of a liver copper value greater than 200 μg of copper per gram dry weight of tissue.

Non-ceruloplasmin copper levels, 64Cu balance studies, and clinical parameters were assessed. No patient developed symptoms of Wilson’s disease in this cohort. Since the cloning and sequencing of the abnormal genes in Wilson’s disease patients, many mutations have been identified that may affect the rate of disease progression. No matched historical control has been compared to this experience, nor has another center replicated this experience.

In a study in the Netherlands, using zinc sulfate, 27 patients were followed up to 29 years by mainly clinical parameters such as tremors, dysarthria, dystonia, ataxia and Kayser-Fleischer rings. No deterioration of the clinical status was observed. In some cases, Kayser-Fleischer rings disappeared and clinical signs and symptoms improved.

Pregnant Patients

Included in a continuing single center United States trial are 19 symptomatic and presymptomatic women who became pregnant and continued Galzin therapy. These women delivered 26 live birth babies. At the time of delivery, the duration of zinc acetate therapy had ranged from 0.7 to 13.7 years. At the time of delivery all patients were using zinc acetate. The zinc acetate dosage at the start of pregnancy ranged from 25 to 50 mg two to three times a day. Two patients were being treated with penicillamine at the start of pregnancy and were switched to zinc acetate during the second month of pregnancy.

Urinary copper excretion was measured to monitor the copper status. Twenty-four hour urine excretion of copper indicated adequate control of copper levels in most patients before and during pregnancies. The results also indicated that during pregnancy, the mothers’ health was protected by zinc acetate therapy, and no adverse effects on liver or neurological functions were reported. Limited pregnancy outcome data indicates an incidence of miscarriages consistent with those in the general population. From this limited experience, the rate of birth defects is 7.7%, while that in the general population is (4%). (See PRECAUTIONS, Pregnancy).

INDICATIONS AND USAGE

Zinc acetate therapy is indicated for maintenance treatment of patients with Wilson’s disease who have been initially treated with a chelating agent (See PRECAUTIONS: Monitoring Patients).

CONTRAINDICATIONS

Zinc Acetate Capsules are contraindicated in patients with known hypersensitivity to any of the components of the formulation.

WARNINGS

Copper Deficiency
Several post-marketing cases reported that zinc acetate taken over extended periods of time (i.e., months to years) may result in decreased enteral copper absorption and copper deficiency. The cases reported the following complications of copper deficiency: anemia, granulocytopenia, leukopenia, neutropenia, pancytopenia, thrombocytopenia, and myeloneuropathy.

If a patient develops signs and/or symptoms of copper deficiency during treatment with zinc acetate, interrupt zinc treatment and measure zinc, 24-hr urinary copper, and non-ceruloplasmin bound copper (NCC) levels. Consider restarting zinc acetate treatment based on periodic monitoring of 24-hr urinary copper and NCC levels.

Gastric Ulcer
There have been postmarketing reports of gastric ulcers with long-term use of zinc acetate. The cases reported the complications of anemia and gastric ulcer perforation with peritonitis. In some cases, ulcers persisted after treatment until zinc acetate was discontinued.

If a patient develops signs and/or symptoms of gastric ulcer during treatment with zinc acetate, discontinue zinc treatment. Most patients showed improvement after cessation of zinc treatment.

PRECAUTIONS

General

Zinc acetate is not recommended for the initial therapy of symptomatic patients because of the delay required for zinc-induced increase in enterocytic metallothionein and blockade of copper uptake. Symptomatic patients should be treated initially, using chelating agents. During initial therapy, neurological deterioration may occur as stores of copper are mobilized. Once initial therapy has been completed, and the patient is clinically stable, maintenance treatment with zinc acetate can be considered, but patients may be continued on initial therapy as clinically indicated.

Information for Patients

Patients should take GALZIN® on an empty stomach, at least one hour before or two to three hours after meals. Capsules should be swallowed whole, not opened or chewed. In the rare event of gastric intolerance of zinc, generally occurring with the morning dose, this dose may be taken between breakfast and lunch. Patients must be clinically monitored to determine the adequacy of zinc acetate therapy. Since strict adherence to the zinc regimen is essential for optimal control of copper distribution and metabolism, the physician must reinforce the need for compliance at each contact with the patient.

Monitoring Patients

Patients should be monitored primarily by assessment of existing signs and symptoms of Wilson’s disease and 24-hour urine copper. Neuropsychiatric evaluations including speech as well as liver function tests including bilirubin and aminotransferases, should be done as appropriate.

The urinary excretion of copper is an accurate reflection of the body status of copper when patients are not on chelation therapy. The clinician should be aware that urinary copper levels are usually increased with chelation therapy such as penicillamine or trientine. Adequate zinc therapy will eventually decrease urinary copper excretion to 125 μg per 24 hours or less. A significant trend upward indicates impending loss of copper control. The non-ceruloplasmin plasma copper (also known as free copper) is obtained by subtracting the ceruloplasmin-bound copper from the total plasma copper. Each mg of ceruloplasmin contains 3 μg of copper. In the United States study, non-ceruloplasmin plasma copper concentration was kept below 20 μg/dL. Urine and plasma for copper determinations should be collected in copper-free containers and assayed with equipment capable of accurately measuring copper at levels as low as 0.01 μg/mL.

An additional monitoring tool, if available, is the amount of radioactivity measured in the plasma 1 or 2 hours after orally administered 64copper. In adequately controlled patients, the amount is less than 1.2% of the administered dose. The level of hepatic copper should not be used to manage therapy since it does not differentiate between potentially toxic free copper and safely bound copper.

In all treated patients, 24-hour urinary zinc levels may be a useful measure of compliance with the zinc acetate regimen.

Drug Interactions

Pharmacodynamic studies in Wilson’s disease patients failed to demonstrate drug interactions between zinc acetate (50 mg t.i.d.) and ascorbic acid (1 g daily), penicillamine (1 g daily), and trientine (1 g daily). Therefore, precautions for zinc acetate effects do not seem necessary when Wilson’s disease patients are taking vitamin C or approved chelating agents. However, no data are available to demonstrate that zinc acetate should be added to other drugs used for the treatment of Wilson’s disease patients or is safe.

Nursing Mothers

Zinc does appear in breast milk and zinc-induced copper deficiency in the nursing baby may occur. Therefore, it is recommended that women on zinc therapy not nurse their babies.

Pediatric Use

Results of observations in a small number of patients in the two clinical trials suggest that pediatric patients aged 10 years and above can be adequately maintained at doses between 75 to 150 mg elemental zinc daily in divided doses. No patients below the age of 10 years have been studied.

Carcinogenesis, Mutagenesis, Impairment of Fertility

Zinc acetate has not been tested for its carcinogenic potential in long-term animal studies, for its mutagenic potential or for its effect on fertility in animals.

However, testing with other salts of zinc (zinc oxide, zinc stearate, zinc sulfate) did not reveal a mutagenicity potential in in vitro Ames assays, and human embryonic lung cell chromosomal aberration assay, and in in vivo rat dominant lethal assay, and rat bone marrow cell chromosomal aberration assay.

Other salts of zinc (zinc oxide, zinc chloride, zinc citrate, zinc maleate, zinc carbonate, zinc sulfate) and pure zinc dust at oral doses up to 326 mg/Kg/day (18 times the recommended human dose based on body surface area) were found to have no effect on fertility and reproductive performance of male and female rats.

Pregnancy: Teratogenic Effects.

Studies in pregnant women have not shown that zinc acetate or zinc sulfate increases the risk of fetal abnormalities if administered during all trimesters of pregnancy. If this drug is used during pregnancy, the possibility of fetal harm appears remote. Because studies cannot rule out the possibility of harm, however, zinc acetate should be used during pregnancy only if clearly needed. While zinc acetate should be used during pregnancy only if clearly needed, copper toxicosis can develop during pregnancy if anti-copper therapy is stopped.

Oral teratology studies have been performed with zinc sulfate in pregnant rats at doses up to 42.5 mg/Kg/day (2 times the recommended human dose based on body surface area), mice at doses up to 30 mg/Kg/day (1 time the recommended human dose based on body surface area), rabbits at doses up to 60 mg/Kg/day (6 times the recommended human dose based on body surface area) and hamsters at doses up to 88 mg/Kg/day (5 times the recommended human dose based on body surface area) and have revealed no evidence of impaired fertility or harm to the fetus due to zinc sulfate. (See CLINICAL TRIALS).

ADVERSE REACTIONS

The following adverse reactions associated with the use of zinc acetate were identified from postmarketing reports. Because these reactions were reported voluntarily from a population of uncertain size, it is not possible to reliably estimate their frequency or establish a causal relationship to drug exposure.

Gastrointestinal disorders: gastric irritation

Investigations: elevations of serum alkaline phosphatase, amylase, and lipase lasting from weeks to months suggesting pancreatitis; the levels usually return to high normal within the first one or two years of zinc therapy.

OVERDOSAGE

Acute oral overdosage with inorganic salts of zinc in humans is reported rarely. In the event of overdosage, the unabsorbed zinc salt should be removed from the stomach by lavage as quickly as possible. The plasma level of zinc should be measured, and heavy metal chelation therapy should be considered if the plasma level of zinc is elevated markedly (>1000 μg/dL). In addition, any signs or symptoms of toxicity should be treated as medically indicated.

One fatality associated with overdosage of zinc sulfate has been reported. The death of this adult woman followed the accidental ingestion of approximately 28 g of zinc sulfate. Death occurred on the fifth day after ingestion and was attributed to renal failure. Hemorrhagic pancreatitis and hyperglycemic coma resulted from the overdose. The amount ingested was 500 mg/Kg of zinc sulfate, a value that is in the same order of magnitude as that found to be lethal in animals.

DOSAGE AND ADMINISTRATION

The recommended adult dose is 50 mg as zinc three times daily (See CLINICAL TRIALS).

Since 25 mg t.i.d. is also an effective dose in children 10 years of age or older or in women who are pregnant, it may be advisable to use a dose of zinc to 25 mg three times a day, as long as the patient is compliant with therapy. The dose can be raised to 50 mg t.i.d. if monitoring indicates a lessening of control (see PRECAUTIONS: Monitoring Patients).

Patients should take zinc acetate on an empty stomach, at least one hour before or two to three hours after meals. For additional information, see PRECAUTIONS.

HOW SUPPLIED

GALZIN®, Zinc Acetate Capsules (25 mg zinc content) are #1 capsules with aqua blue opaque cap and body, imprinted "93-215." Packaged in bottles of 250 (NDC 71863-124-25).

GALZIN® Zinc Acetate Capsules (50 mg zinc content) are #1 capsules with orange opaque cap and body, imprinted "93-208." Packaged in bottles of 250 (NDC 71863-125-25).

Store at USP Controlled Room Temperature 20°C to 25°C (68°F to 77°F); excursions permitted to 15°C to 30°C (59°F to 86°F). Dispense in a tight, light-resistant container as defined in the USP, with a child-resistant closure.

Rx only.
Revised: 09/2025

Distributed by:

Eton Pharmaceuticals, Inc. Deer Park, IL 60010
©2025 Eton Pharmaceuticals, Inc. All rights reserved.

PL-57-2.0

PRINCIPAL DISPLAY PANEL

Galzin 25 mg - NDC 71863-124-25 - 250 Capsules Bottle Label

Galzin 50 mg - NDC 71863-125-25 - 250 Capsules Bottle Label